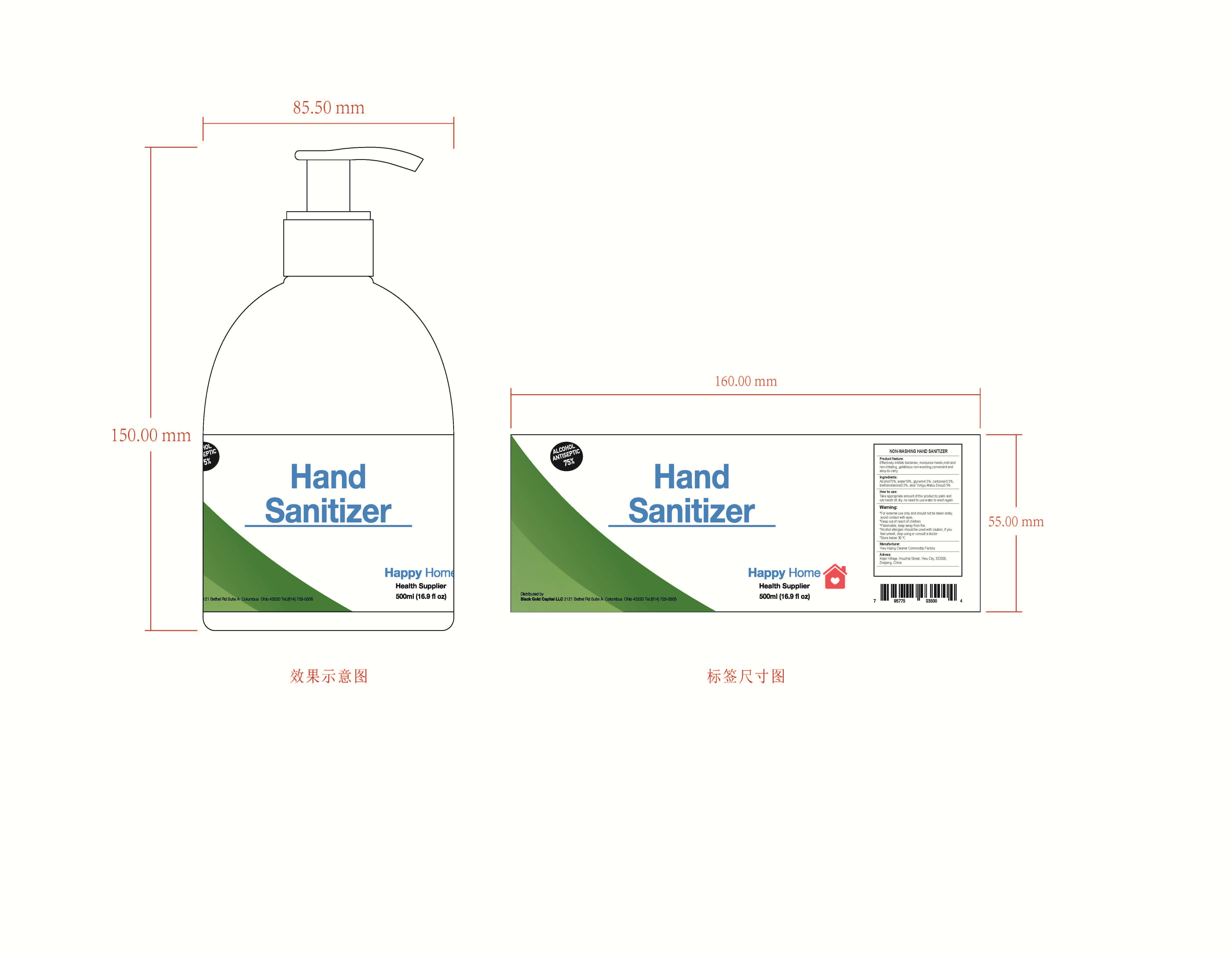 DRUG LABEL: NON-WASHING HAND SANITIZER
NDC: 52687-004 | Form: LIQUID
Manufacturer: Yiwu Kejing Cleaning Products Factory
Category: otc | Type: HUMAN OTC DRUG LABEL
Date: 20200430

ACTIVE INGREDIENTS: ALCOHOL 375 mL/500 mL
INACTIVE INGREDIENTS: CARBOMER HOMOPOLYMER, UNSPECIFIED TYPE; TROLAMINE; WATER; ALOE; GLYCERIN

DOSAGE AND ADMINISTRATION

Store below 30 °

keep out of reach of children section

WARNINGS

*For external use only and should not be taken orally, avoid contact with eyes.

*Keep out of reach of children.

*Flammable, keep away from fire.

*Alcohol allergies should be used with caution, if you feel unwell, stop using or consult a doctor.

*Store below 30°C.

PURPOSE

Disinfection
Sterilization
No Rinseing

ACTIVE INGREDIENT

Alcohol

INACTIVE INGREDIENT

water

glycerin

carbomer

triethanolamine

aloe Yohjyu Matsu Ekisu

INDICATIONS AND USAGE

Take appropriate amount of this product to palm and rub hands till dry, no need to use water to wash again.